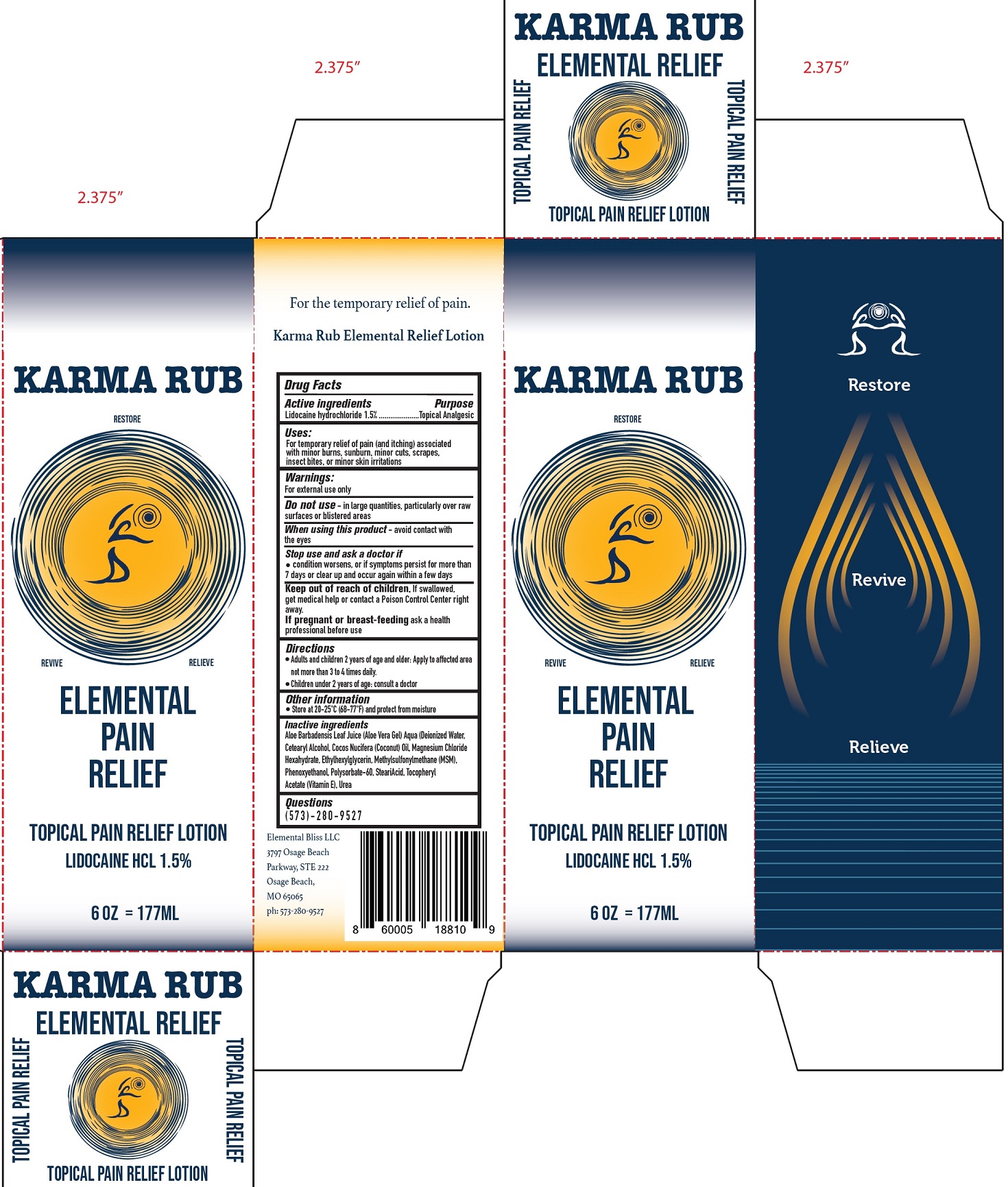 DRUG LABEL: KARMA RUB Elemental Pain Relief
NDC: 81155-104 | Form: LOTION
Manufacturer: Elemental Bliss LLC
Category: otc | Type: HUMAN OTC DRUG LABEL
Date: 20231111

ACTIVE INGREDIENTS: LIDOCAINE HYDROCHLORIDE 15 mg/1 mL
INACTIVE INGREDIENTS: ALOE VERA LEAF; WATER; CETOSTEARYL ALCOHOL; COCONUT OIL; MAGNESIUM CHLORIDE; ETHYLHEXYLGLYCERIN; DIMETHYL SULFONE; PHENOXYETHANOL; POLYSORBATE 60; STEARIC ACID; .ALPHA.-TOCOPHEROL ACETATE; UREA

KARMA RUB Elemental Pain Relief Lotion

Active ingredients

Lidocaine hydrochloride 1.5%

Purpose

Topical Analgesic

Uses:

For temporary relief of pain (and itching) associated with minor burns, sunburn, minor cuts, scrapes, insect bites, or minor skin irritations

Warnings:

For external use only

Do not use

- in large quantities, particularly over raw surfaces or blistered areas

When using this product

- avoid contact with the eyes

Stop use and ask a doctor if

- condition worsens, or if symptoms persist for more than 7 days or clear up and occur again within a few days

Keep out of reach of children.

If swallowed, get medical help or contact a Poison Control Center right away.

If pregnant or breast-feeding

ask a health professional before use

Other information

- Adults and children 2 years of age and older: Apply to affected area not more than 3 to 4 times daily.
- Children under 2 years of age: consult a doctor

Other information

- Store at 20-25°C (68-77°F) and protect from moisture

Inactive ingredients

Aloe Barbadensis Leaf Juice (Aloe Vera Gel) Aqua (Deionized Water, Cetearyl Alcohol, Cocos Nucifera (Coconut) Oil, Magnesium Chloride Hexahydrate, Ethylhexylglycerin, Methylsulfonylmethane (MSM), Phenoxyethanol, Polysorbate-60, SteariAcid, Tocopheryl Acetate (Vitamin E), Urea

Questions

(5 7 3) - 2 8 0 - 9 5 2 7